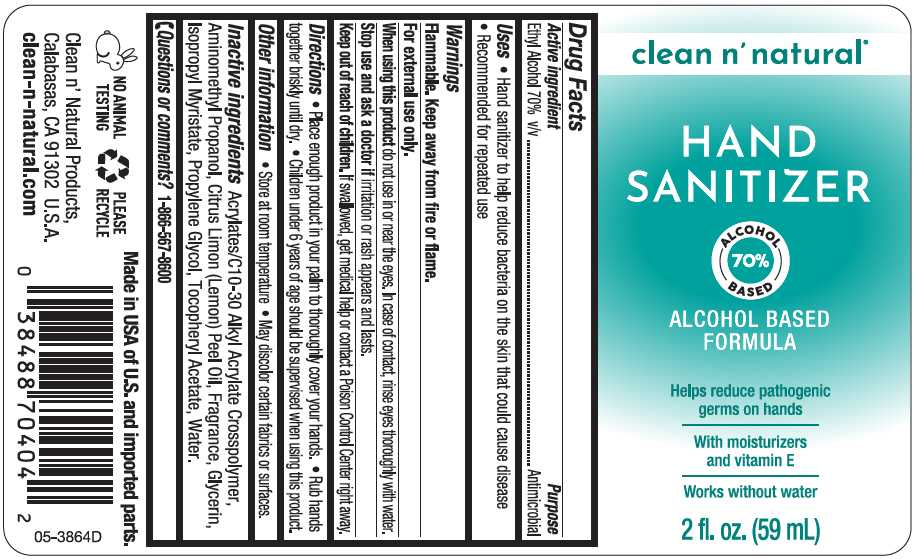 DRUG LABEL: clean n natural Hand Sanitizer 
NDC: 67385-026 | Form: GEL
Manufacturer: Garcoa, Inc.
Category: otc | Type: HUMAN OTC DRUG LABEL
Date: 20220127

ACTIVE INGREDIENTS: Alcohol 700 mg/1 mL
INACTIVE INGREDIENTS: CARBOMER INTERPOLYMER TYPE A (ALLYL SUCROSE CROSSLINKED); AMINOMETHYLPROPANOL; LEMON OIL, COLD PRESSED; Glycerin; Isopropyl Myristate; Propylene Glycol; .ALPHA.-TOCOPHEROL ACETATE, DL-; Water

clean n' natural® Hand Sanitizer
Antimicrobial

Drug Facts

Active ingredient

Ethyl Alcohol 70% v/v

Purpose

Antimicrobial

Uses

⬥ Hand sanitizer to help reduce bacteria on the skin that could cause disease
⬥ Recommended for repeated use

Warnings

Flammable. Keep away from fire or flame.

For external use only.

When using this product do not use in or near the eyes. In case of contact, rinse eyes thoroughly with water.

Stop use and ask a doctor if irritation or rash appears and lasts..

Keep out of reach of children. If swallowed, get medical help or contact a Poison Control Center (1-800-222-1222) right away.

Directions

⬥ place enough product in your palm to thoroughly cover your hands
⬥ Rub hands together briskly until dry.
⬥ Children under 6 years of age should be supervised when using this product.

Other information

⬥ Store at room temperature
⬥ May discolor certain fabrics or surfaces.

Inactive ingredients

Acrylates/C10-30 Alkyl Acrylate Crosspolymer, Aminomethyl Propanol, Citrus Limon (Lemon) Peel Oil, Fragrance, Glycerin, Isopropyl Myristate, Propylene Glycol, Tocopheryl Acetate, Water

Questions or comments?

1-866-567-8600

PRINCIPAL DISPLAY PANEL - 59 mL Bottle Label

clean n' natural®

HAND
SANITIZER

ALCOHOL
70%
BASED

ALCOHOL BASED
FORMULA

Helps reduce pathogenic
germs on hands

With moisturizers
and vitamin E

Works without water

2 fl. oz. (59 mL)